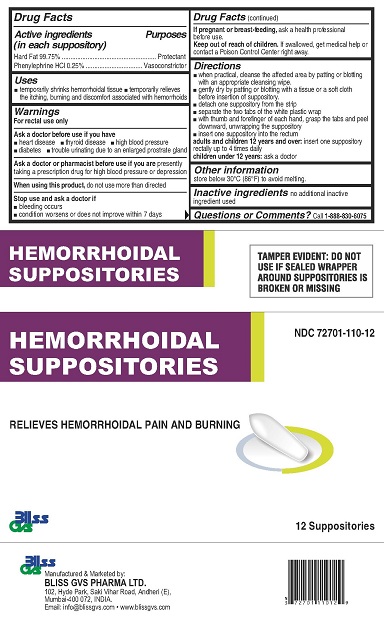 DRUG LABEL: Bliss GVS Hemorrhoidal
NDC: 72701-110 | Form: SUPPOSITORY
Manufacturer: Bliss GVS Pharma Limited
Category: otc | Type: HUMAN OTC DRUG LABEL
Date: 20241219

ACTIVE INGREDIENTS: HARD FAT 2493.75 mg/1 1; PHENYLEPHRINE HYDROCHLORIDE 6.25 mg/1 1

BLISS HEMORRHOIDAL SUPPOSITORIES

Active ingredients

(in each suppository)

Hard Fat 99.75%

Phenylephrine HCl 0.25%

Purposes

Protectant

Vasoconstrictor

Uses

- temporarily shrinks hemorrhoidal tissue
- temporarily relieves the itching, burning and discomfort associated with hemorrhoids

Warnings

For rectal use only

Ask a doctor before use if you have

- heart disease
- thyroid disease
- high blood pressure
- diabetes
- trouble urinating due to an enlarged prostate gland

Ask a doctor or pharmacist before use if you arepresently taking a prescription drug for high blood pressure or depression.

WHEN USING

When using this productdo not use more than directed

Stop use and ask a doctor if

- bleeding occurs
- condition worsens or does not improve within 7 days

PREGNANCY OR BREAST FEEDING

If pregnant or breast-feeding,ask a health professional before use.

Keep out of reach of children.If swallowed, get medical help or contact a Poison Control Center right away.

Directions

- when practical, cleanse the affected area by patting or blotting with an appropriate cleansing wipe.
- gently dry by patting or blotting with a tissue or a soft cloth before insertion of suppository.
- detach one suppository from the strip
- separate the two tabs of the white plastic wrap
- with thumb and forefinger of each hand, grasp the tabs and peel downward, unwrapping the suppository
- insert one suppository into the rectum

adults and children 12 years and over:insert one suppository rectally up to 4 times daily

children under 12 years:ask a doctor

Other information

store below 30°C (86°F) to avoid melting.

Inactive ingredients

none

Questions or Comments?

Call 1-888-830-6075

TAMPER EVIDENT: DO NOT USE IF SEALED WRAPPER AROUND SUPPOSITORIES IS BROKEN OR MISSING

Manufactured and Marketed by:

BLISS GVS PHARMA LTD.

102, Hyde Park, Saki Vihar Road, Andheri (E),

Mumbai-400 072, INDIA

Email: info@blissgvs.com • www.blissgvs.com

PACKAGE LABEL

HEMORRHOIDAL SUPPOSITORIES

NDC 72701-110-12

RELIEVES HEMORRHOIDAL PAIN AND BURNING

Bliss GVS

12 Suppositories